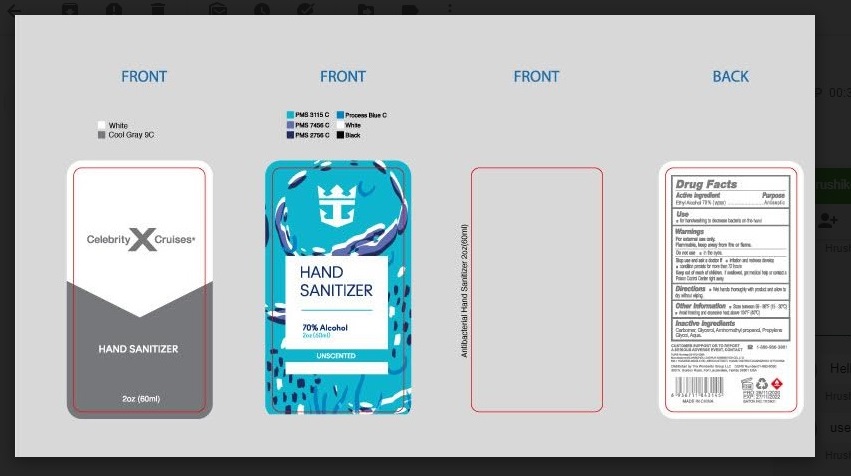 DRUG LABEL: Anti-Bacterial Hand Sanitizer
NDC: 77027-113 | Form: GEL
Manufacturer: GUANGZHOU ZUOFUN COSMETICS CO., LTD.
Category: otc | Type: HUMAN OTC DRUG LABEL
Date: 20211124

ACTIVE INGREDIENTS: ALCOHOL 70 mL/100 mL
INACTIVE INGREDIENTS: WATER; PROPYLENE GLYCOL; GLYCERIN; CARBOMER HOMOPOLYMER, UNSPECIFIED TYPE; AMINOMETHYLPROPANOL

Anti-Bacterial Hand Sanitizer

Active ingredient

Ethyl Alcohol 70%

Purpose

Antiseptic

Uses

- for handwashing to decrease bacteria on the hand

Warnings

- For external use only
- Flammable, keep away from fire or flame
- Do not use in the eyes

Stop use and ask a doctor if:

- Irritation and redness develop
- Condition presists more than 72 hours

Keep out of reach of children.

- If swallowed, get medical help or contact Poison Control Center right away.

Directions

Wet hands thoroughly with product and allow to dry without wiping.

Other Information

Store between 59-86°F (15-30°C)

Avoid freezing and excessive heat above 104°F (40°C)

Inactive ingredients

Carbomer, Glycerol, Aminomethyl Propanol, Propylene Glycol , Aqua.